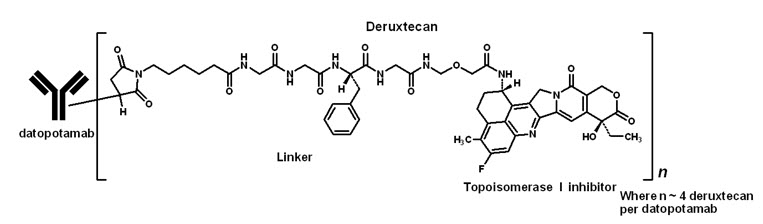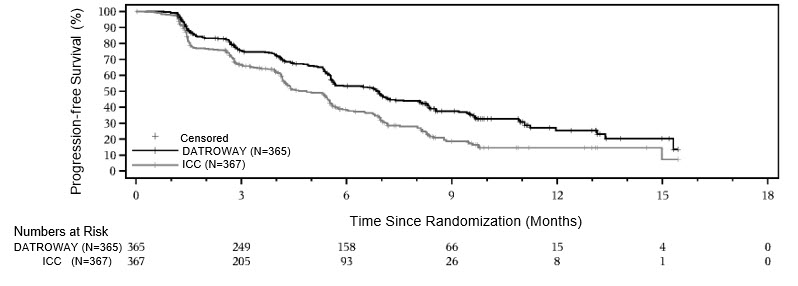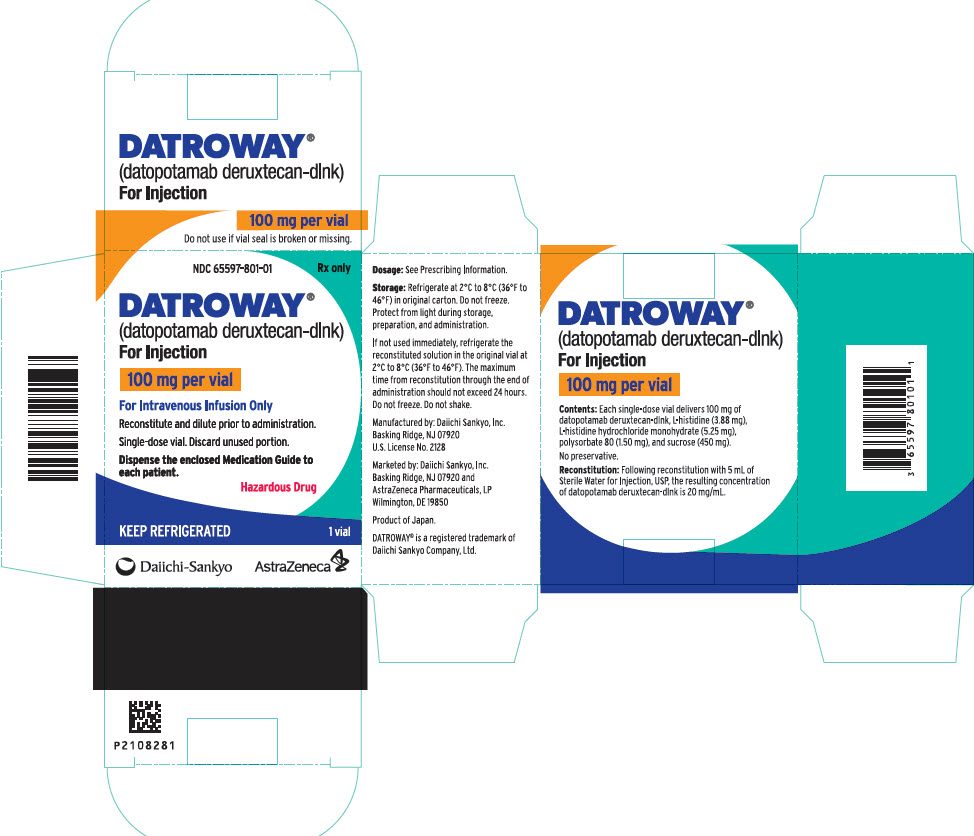 DRUG LABEL: DATROWAY
NDC: 65597-801 | Form: INJECTION, POWDER, LYOPHILIZED, FOR SOLUTION
Manufacturer: Daiichi Sankyo Inc.
Category: prescription | Type: HUMAN PRESCRIPTION DRUG LABEL
Date: 20260105

ACTIVE INGREDIENTS: DATOPOTAMAB DERUXTECAN 100 mg/5 mL
INACTIVE INGREDIENTS: HISTIDINE; HISTIDINE HYDROCHLORIDE MONOHYDRATE; SUCROSE; POLYSORBATE 80

HIGHLIGHTS OF PRESCRIBING INFORMATION

These highlights do not include all the information needed to use DATROWAY safely and effectively. See full prescribing information for DATROWAY.
DATROWAY® (datopotamab deruxtecan-dlnk) for injection, for intravenous use
Initial U.S. Approval: 2025

1 INDICATIONS AND USAGE

DATROWAY is a Trop-2-directed antibody and topoisomerase inhibitor conjugate indicated for the treatment of:

- adult patients with locally advanced or metastatic epidermal growth factor receptor (EGFR)-mutated non-small cell lung cancer (NSCLC) who have received prior EGFR-directed therapy and platinum-based chemotherapy. (1.1)
  This indication is approved under accelerated approval based on objective response rate and duration of response [see Clinical Studies (14.1)]. Continued approval for this indication may be contingent upon verification and description of clinical benefit in the confirmatory trial.
- adult patients with unresectable or metastatic, hormone receptor (HR)-positive, human epidermal growth factor receptor 2 (HER2)-negative (IHC 0, IHC 1+ or IHC 2+/ISH-) breast cancer who have received prior endocrine-based therapy and chemotherapy for unresectable or metastatic disease. (1.2)

2 DOSAGE AND ADMINISTRATION

- Reconstitute DATROWAY with Sterile Water for Injection. (2.5)
- Dilute with 5% Dextrose Injection. (2.5)
- For intravenous infusion only. Do not administer as an intravenous push or bolus. DO NOT use Sodium Chloride Injection, USP. (2.5)
- Premedicate to reduce the risk of infusion reactions and nausea and vomiting. (2.3)
- The recommended dosage of DATROWAY is 6 mg/kg (up to a maximum of 540 mg for patients ≥90 kg) given as an intravenous infusion once every 3 weeks (21-day cycle) until disease progression or unacceptable toxicity. (2.3, 2.4)

3 DOSAGE FORMS AND STRENGTHS

For injection: 100 mg lyophilized powder in a single-dose vial. (3)

4 CONTRAINDICATIONS

None. (4)

5 WARNINGS AND PRECAUTIONS

- Interstitial Lung Disease (ILD) and Pneumonitis: DATROWAY can cause severe and fatal cases of ILD/pneumonitis. Monitor for new or worsening signs and symptoms of ILD/pneumonitis. If ILD/pneumonitis is suspected, withhold DATROWAY and initiate corticosteroids. Permanently discontinue DATROWAY in patients with confirmed Grade 2 or higher ILD/pneumonitis. (5.1)
- Ocular Adverse Reactions: DATROWAY can cause ocular adverse reactions including dry eye, keratitis, blepharitis, meibomian gland dysfunction, increased lacrimation, conjunctivitis, and blurred vision. Monitor patients for ocular adverse reactions during treatment with DATROWAY. Advise patients to use preservative-free lubricating eye drops and to avoid using contact lenses during treatment with DATROWAY. Withhold, reduce the dose, or permanently discontinue DATROWAY based on the severity of ocular adverse reactions. Refer patients to an eye care professional for any new or worsening ocular signs and symptoms. (2.3, 2.4, 5.2)
- Stomatitis/Oral Mucositis: DATROWAY can cause stomatitis, including mouth ulcers and oral mucositis. Advise patients to use a steroid-containing mouthwash when starting treatment and to hold ice chips or ice water in mouth during the infusion of DATROWAY. Withhold, reduce the dose, or permanently discontinue DATROWAY based on severity. (2.3, 2.4, 5.3)
- Embryo-Fetal Toxicity: DATROWAY can cause fetal harm. Advise patients of potential risk to a fetus and to use effective contraception. (5.4, 8.1, 8.3)

6 ADVERSE REACTIONS

The most common adverse reactions (≥20%), including laboratory abnormalities, in patients with:

- EGFR-mutated NSCLC were stomatitis, nausea, alopecia, fatigue, decreased hemoglobin, decreased lymphocytes, constipation, increased calcium, increased AST, decreased white blood cell count, increased lactate dehydrogenase, musculoskeletal pain, decreased appetite, increased ALT, and rash. (6.1)
- HR-positive, HER2-negative breast cancer were stomatitis, nausea, fatigue, decreased leukocytes, decreased calcium, alopecia, decreased lymphocytes, decreased hemoglobin, constipation, decreased neutrophils, dry eye, vomiting, increased ALT, keratitis, increased AST, and increased alkaline phosphatase. (6.1)

To report SUSPECTED ADVERSE REACTIONS, contact Daiichi Sankyo, Inc. at 1-877-437-7763 or FDA at 1-800-FDA-1088 or www.fda.gov/medwatch.

8 USE IN SPECIFIC POPULATIONS

- Lactation: Advise not to breastfeed. (8.2)
- Infertility: May impair fertility in males and females. (8.3)

FULL PRESCRIBING INFORMATION

1 INDICATIONS AND USAGE

1.1 Locally Advanced or Metastatic EGFR-Mutated Non-Small Cell Lung Cancer (NSCLC)

DATROWAY is indicated for the treatment of adult patients with locally advanced or metastatic epidermal growth factor receptor (EGFR)-mutated non-small cell lung cancer (NSCLC) who have received prior EGFR-directed therapy and platinum-based chemotherapy.

This indication is approved under accelerated approval based on objective response rate and duration of response [see Clinical Studies (14.1)]. Continued approval for this indication may be contingent upon verification and description of clinical benefit in the confirmatory trial.

1.2 Unresectable or Metastatic, HR-Positive, HER2-Negative Breast Cancer

DATROWAY is indicated for the treatment of adult patients with unresectable or metastatic, hormone receptor (HR)-positive, human epidermal growth factor receptor 2 (HER2)-negative (IHC 0, IHC 1+ or IHC 2+/ISH-) breast cancer who have received prior endocrine-based therapy and chemotherapy for unresectable or metastatic disease.

2 DOSAGE AND ADMINISTRATION

2.1 Patient Selection

Select patients with locally advanced or metastatic NSCLC for treatment with DATROWAY based on the presence of epidermal growth factor receptor (EGFR) mutations in tumor or plasma specimens [see Clinical Studies (14.1)]. Testing may be performed at any time from initial diagnosis and does not need to be repeated once EGFR mutation status has been established.

2.2 Recommended Dosage

The recommended dosage of DATROWAY is 6 mg/kg (up to a maximum of 540 mg for patients ≥90 kg) administered as an intravenous infusion once every 3 weeks (21-day cycle) until disease progression or unacceptable toxicity.

If a planned dose is delayed or missed, administer as soon as possible; do not wait until the next planned cycle. Adjust the schedule of administration to maintain a 3-week interval between doses.

2.3 Premedication, Concomitant Medications, and Required Eye Care

Conduct an ophthalmic exam including visual acuity testing, slit lamp examination (with fluorescein staining), intraocular pressure, and fundoscopy at initiation of DATROWAY, annually while on treatment, at end of treatment, and as clinically indicated.

Administer DATROWAY with the premedication and concomitant medications described in Table 1.

Monitor patients for infusion-related reactions in a setting where cardiopulmonary resuscitation medication and equipment are available. Monitor patients for at least 1 hour for the first 2 cycles of DATROWAY infusions. If there are no infusion-related reactions observed, monitor patients for at least 30 minutes for all subsequent cycles of infusions.

Table 1: Premedication and Concomitant Medications
Premedication [With or without systemic corticosteroid] | Examples (or equivalent) | Timing of Treatment/Duration
Eye drops [see Warnings and Precautions (5.2)] | Preservative-free lubricant eye drops | Administer at least four times daily and as needed
Mouthwash [see Warnings and Precautions (5.3)] | Steroid-containing mouthwash (dexamethasone oral solution 0.1 mg/mL) | Administer four times daily and as needed
Antihistamine [see Adverse Reactions (6.1)] | Diphenhydramine (25 to 50 mg) administered intravenously or orally | Administer 30-60 minutes prior to each infusion
Antipyretic [see Adverse Reactions (6.1)] | Acetaminophen (650 to 1,000 mg) administered intravenously or orally | Administer 30-60 minutes prior to each infusion
Antiemetics [see Adverse Reactions (6.1)] | 5-HT3 serotonin receptor antagonist or appropriate alternatives intravenously or oral | Prior to each infusion and thereafter as needed

2.4 Dosage Modifications

Dosage Modifications for Adverse Reactions

The recommended dose reduction levels for adverse reactions are described in Table 2.

Table 2: Recommended Dosage Reductions of DATROWAY for Adverse Reactions
Dose Reductions | Recommended Dose
First | 4 mg/kg (up to a maximum of 360 mg for patients ≥90 kg)
Second | 3 mg/kg (up to a maximum of 270 mg for patients ≥90 kg)
Third | Permanently discontinue

Do not re-escalate the DATROWAY dose after a dose reduction. Permanently discontinue DATROWAY in patients who are unable to tolerate 3 mg/kg intravenously once every 3 weeks.

The recommended dosage modifications and management of adverse reactions for DATROWAY are described in Table 3.

Table 3: Dosage Modifications and Management of Adverse Reactions for DATROWAY
Adverse Reaction | Severity [Toxicity grades are in accordance with National Cancer Institute Common Terminology Criteria for Adverse Events (NCI CTCAE) version 5.0.] | Dosage Modifications
Interstitial Lung Disease (ILD)/Pneumonitis [see Warnings and Precautions (5.1)] | Asymptomatic ILD/pneumonitis Grade 1 | Withhold DATROWAY until ILD/pneumonitis is completely resolved, then:; - if resolved in ≤28 days, maintain current dose. - if resolved in >28 days, reduce one dose level (see Table 2). - Consider corticosteroids as soon as ILD/pneumonitis is suspected.
Interstitial Lung Disease (ILD)/Pneumonitis [see Warnings and Precautions (5.1)] | Symptomatic ILD/pneumonitis Grade 2 or greater | - Permanently discontinue DATROWAY. - Administer corticosteroids as soon as ILD/pneumonitis is suspected.
Keratitis [see Warnings and Precautions (5.2) and Adverse Reactions (6.1)] | Nonconfluent superficial keratitis | - Monitor. - Continue DATROWAY at current dose.
 | Confluent superficial keratitis, a cornea epithelial defect, or 3-line or more loss in best corrected visual acuity | - Withhold DATROWAY until improved or resolved - Restart DATROWAY at the same dose level or consider dose reduction (see Table 2).
 | Corneal ulcer or stromal opacity or best corrected distance visual acuity 20/200 or worse | - Withhold DATROWAY until improved or resolved - Restart DATROWAY at reduced dose level (see Table 2).
 | Corneal perforation | - Permanently discontinue DATROWAY.
Stomatitis [see Warnings and Precautions (5.3)] | Grade 1 | - Optimize prophylactic and supportive medications. - Continue DATROWAY at current dose.
Stomatitis [see Warnings and Precautions (5.3)] | Grade 2 | - Withhold DATROWAY until resolved to ≤Grade 1. - Restart DATROWAY at the same dose level for first occurrence. - Recurrence: consider restarting at reduced dose level (see Table 2).
Stomatitis [see Warnings and Precautions (5.3)] | Grade 3 | - Withhold DATROWAY until resolved to ≤Grade 1. - Restart DATROWAY at reduced dose level (see Table 2).
Stomatitis [see Warnings and Precautions (5.3)] | Grade 4 | - Permanently discontinue DATROWAY.
Infusion-Related Reactions (IRR) [see Adverse Reactions (6.1)] | Grade 1 | - Reduce DATROWAY infusion rate by 50% if IRR is suspected and monitor patient closely.
Infusion-Related Reactions (IRR) [see Adverse Reactions (6.1)] | Grade 2 | - Interrupt DATROWAY infusion and administer supportive care medications. - If the event resolves or improves to Grade 1, restart the infusion at 50% rate. - Administer all subsequent infusions at the reduced rate.
Infusion-Related Reactions (IRR) [see Adverse Reactions (6.1)] | Grade 3 or 4 | - Permanently discontinue DATROWAY.
Other Non-Hematologic Adverse Reactions [see Adverse Reactions (6.1)] | Grade 3 | - Withhold dose until resolved to ≤Grade 1 or baseline - Restart DATROWAY at reduced dose level (see Table 2).
Other Non-Hematologic Adverse Reactions [see Adverse Reactions (6.1)] | Grade 4 | - Permanently discontinue DATROWAY.

2.5 Preparation and Administration

Reconstitute and further dilute DATROWAY prior to intravenous infusion. Use appropriate aseptic technique.

DATROWAY (datopotamab deruxtecan-dlnk) is a hazardous drug. Follow applicable special handling and disposal procedures.^1

Reconstitution

- Reconstitute immediately before dilution.
- More than one vial may be needed for a full dose. Calculate the dose (mg), the total volume of reconstituted DATROWAY solution required, and the number of vial(s) of DATROWAY needed [see Dosage and Administration (2.2)].
- Reconstitute each 100 mg vial using a sterile syringe to slowly inject 5 mL of Sterile Water for Injection into each vial to obtain a final concentration of 20 mg/mL.
- Swirl the vial gently until completely dissolved. Do not shake.
- If not used immediately, refrigerate the reconstituted DATROWAY solution in the original vial at 2ºC to 8ºC (36°F to 46°F) for up to 24 hours from the time of reconstitution. Protect the vial from light. Do not freeze.
- The product does not contain a preservative. Discard unused reconstituted DATROWAY after 24 hours refrigerated.

Dilution

- Withdraw the calculated amount from the vial(s) using a sterile syringe. Inspect for particulate matter and discoloration prior to administration. The reconstituted solution should be clear and colorless to light yellow. Do not use if visible particles are observed or if the solution is cloudy or discolored.
- Dilute the calculated volume of reconstituted DATROWAY in an infusion bag containing 100 mL of 5% Dextrose Injection. DO NOT use Sodium Chloride Injection. DATROWAY is compatible with an infusion bag made of polyvinylchloride or polyolefin (polypropylene or copolymer of ethylene and propylene).
- Gently invert the infusion bag to thoroughly mix the solution. Do not shake.
- Cover the infusion bag to protect from light.
- If not used immediately, store at room temperature at up to 25ºC (77°F) for up to 4 hours including preparation or in a refrigerator at 2ºC to 8ºC (36°F to 46°F) for up to 24 hours. Do not freeze.
- Discard any unused portion left in the vial.

Administration

- The maximum time from reconstitution of the vial through the end of administration should not exceed 24 hours. Discard if storage time exceeds these limits.
- If the prepared infusion solution was stored refrigerated at 2ºC to 8ºC (36°F to 46°F), allow the solution to reach room temperature prior to administration, protected from light.
- Inspect for particulate matter and discoloration prior to administration.
- Administer DATROWAY as an intravenous infusion only with an infusion line and tubing set made of polyvinyl chloride, polybutadiene or low-density polyethylene.
- Administer DATROWAY with a 0.2-micron in-line polytetrafluoroethylene, polyethersulfone or nylon 66 filter.
- Do NOT administer as an intravenous push or bolus.
- Cover the infusion bag to protect from light during administration.
- Do not mix DATROWAY with other drugs or administer other drugs through the same intravenous line.
- Instruct the patient to hold ice chips or ice water in the mouth throughout the infusion of DATROWAY.
- First infusion: Administer infusion over 90 minutes. Observe patients during the infusion and for at least 1 hour following the initial dose for signs or symptoms of infusion-related reactions.
- Second Infusion: If first infusion was tolerated, administer second infusion over 30 minutes. Observe patients during the infusion and for at least 1 hour after infusion.
- Subsequent Infusions: Administer infusion over 30 minutes if prior infusions were tolerated. Observe patients during the infusion and for at least 30 min after infusion.

3 DOSAGE FORMS AND STRENGTHS

For injection: 100 mg of datopotamab deruxtecan-dlnk as a white to yellowish white, lyophilized powder in a single-dose vial for reconstitution and further dilution.

4 CONTRAINDICATIONS

None.

5 WARNINGS AND PRECAUTIONS

5.1 Interstitial Lung Disease/Pneumonitis

DATROWAY can cause severe, life-threatening, or fatal interstitial lung disease (ILD) or pneumonitis.

Locally Advanced or Metastatic NSCLC

In the pooled safety population of 484 patients with NSCLC from TROPION-Lung01, TROPION-Lung05, and TROPION-PanTumor01 [see Adverse Reactions (6.1)], ILD/pneumonitis occurred in 7% of patients treated with DATROWAY, including 0.6% of patients with Grade 3 and 0.4% with Grade 4. There were 8 (1.7%) fatal cases. The median time to onset for ILD was 1.4 months (range: 0.2 months to 9 months). Eleven patients (2.3%) had DATROWAY withheld and 20 patients (4.1%) permanently discontinued DATROWAY due to ILD/pneumonitis. Systemic corticosteroids were required in 79% (26/33) of patients with ILD/pneumonitis. ILD/pneumonitis resolved in 45% of patients.

Unresectable or Metastatic Breast Cancer

In the pooled safety population of 443 patients with breast cancer from TROPION-Breast01 and TROPION-PanTumor01 [see Adverse Reactions (6.1)], ILD/pneumonitis occurred in 3.6% of patients treated with DATROWAY, including 0.7% of patients with Grade 3. There was one fatal case (0.2%). The median time to onset for ILD was 2.8 months (range: 1.1 months to 10.8 months). Four patients (0.9%) had DATROWAY withheld and 7 patients (1.6%) permanently discontinued DATROWAY due to ILD/pneumonitis. Systemic corticosteroids were required in 60% (9/15) of patients with ILD/pneumonitis. ILD/pneumonitis resolved in 40% of patients.

Patients were excluded from clinical studies for a history of ILD/pneumonitis requiring treatment with steroids or for ongoing ILD/pneumonitis.

Monitor patients for new or worsening respiratory symptoms indicative of ILD/pneumonitis (e.g., dyspnea, cough, fever) during treatment with DATROWAY. For asymptomatic (Grade 1) ILD/pneumonitis, consider corticosteroid treatment (e.g., ≥0.5 mg/kg/day prednisolone or equivalent). For symptomatic ILD/pneumonitis (Grade 2 or greater), promptly initiate systemic corticosteroid treatment (e.g., ≥1 mg/kg/day prednisolone or equivalent) and continue for at least 14 days followed by gradual taper for at least 4 weeks.

Withhold DATROWAY in patients with suspected ILD/pneumonitis and permanently discontinue DATROWAY if ≥Grade 2 ILD/pneumonitis is confirmed [see Dosage and Administration (2.4)].

5.2 Ocular Adverse Reactions

DATROWAY can cause ocular adverse reactions including dry eye, keratitis, blepharitis, meibomian gland dysfunction, increased lacrimation, conjunctivitis, and blurred vision.

In the pooled safety population [see Adverse Reactions (6.1)], ocular adverse reactions occurred in 36% of patients treated with DATROWAY. Twenty patients (2.2%) experienced Grade 3 ocular adverse reactions, which included keratitis, dry eye, and blurred vision, and one patient experienced a Grade 4 ocular adverse reaction of conjunctival hemorrhage. The most common (≥5%) ocular adverse reactions were dry eye (17%), keratitis (14%), and increased lacrimation (7%). The median time to onset for ocular adverse reactions was 2.3 months (range: 0.03 months to 23.2 months). Of the patients who experienced ocular adverse reactions, 39% had complete resolution, and 10% had partial improvement (defined as a decrease in severity by one or more grades from the worst grade at last follow up). Ocular adverse reactions led to dosage interruption in 3.6% of patients, dosage reductions in 2.5% of patients, and permanent discontinuation of DATROWAY in 1% of patients.

Patients with clinically significant corneal disease were excluded from clinical studies.

Advise patients to use preservative-free lubricant eye drops several times daily for prophylaxis. Advise patients to avoid use of contact lenses unless directed by an eye care professional.

Refer patients to an eye care professional for an ophthalmic exam including visual acuity testing, slit lamp examination (with fluorescein staining), intraocular pressure, and fundoscopy at treatment initiation, annually while on treatment, at end of treatment, and as clinically indicated.

Promptly refer patients to an eye care professional for any new or worsening ocular adverse reactions. Monitor patients for ocular adverse reactions during treatment with DATROWAY, and if diagnosis is confirmed, withhold, reduce the dose, or permanently discontinue DATROWAY based on severity [see Dosage and Administration (2.4)].

5.3 Stomatitis

DATROWAY can cause stomatitis, including mouth ulcers and oral mucositis.

In the pooled safety population [see Adverse Reactions (6.1)], stomatitis occurred in 63% of patients treated with DATROWAY, including 8% of patients with Grade 3 events and one patient with a Grade 4 reaction. The median time to first onset of stomatitis was 0.5 months (range: 0.03 months to 18.6 months). Stomatitis led to dosage interruption in 6% of patients, dosage reductions in 11% of patients, and permanent discontinuation of DATROWAY in 0.5% of patients.

In patients who received DATROWAY in TROPION-Breast01, 39% used a mouthwash containing corticosteroid for management or prophylaxis of stomatitis/oral mucositis at any time during the treatment.

Advise patients to use a steroid-containing mouthwash for prophylaxis and treatment of stomatitis. Instruct the patient to hold ice chips or ice water in the mouth throughout the infusion of DATROWAY.

Monitor patients for signs and symptoms of stomatitis. If stomatitis occurs, increase the frequency of mouthwash and administer other topical treatments as clinically indicated. Based on the severity of the adverse reaction, withhold, reduce the dose, or permanently discontinue DATROWAY [see Dosage and Administration (2.4)].

5.4 Embryo-Fetal Toxicity

Based on its mechanism of action, DATROWAY can cause embryo-fetal harm when administered to a pregnant woman because the topoisomerase inhibitor component of DATROWAY, DXd [see Description (11)], is genotoxic and affects actively dividing cells [see Use in Specific Populations (8.1), Clinical Pharmacology (12.1), Nonclinical Toxicology (13.1)].

Advise patients of the potential risk to a fetus. Advise female patients of reproductive potential to use effective contraception during treatment with DATROWAY and for 7 months after the last dose. Advise male patients with female partners of reproductive potential to use effective contraception during treatment with DATROWAY and for 4 months after the last dose [see Use in Specific Populations (8.1, 8.3)].

6 ADVERSE REACTIONS

The following clinically significant adverse reactions are described elsewhere in the labeling:

- Interstitial Lung Disease/Pneumonitis [see Warnings and Precautions (5.1)]
- Ocular Adverse Reactions [see Warnings and Precautions (5.2)]
- Stomatitis [see Warnings and Precautions (5.3)]

6.1 Clinical Trials Experience

Because clinical trials are conducted under widely varying conditions, adverse reaction rates observed in the clinical trials of a drug cannot be directly compared to rates in the clinical trials of another drug and may not reflect the rates observed in practice.

The pooled safety population described in WARNINGS AND PRECAUTIONS reflects exposure to DATROWAY in 927 patients as a single agent at 6 mg/kg administered as an intravenous infusion once every 3 weeks (21-day cycle) until disease progression or unacceptable toxicity. This included 137 patients with NSCLC in TROPION-Lung05 [see Clinical Studies (14.1)], 297 patients with NSCLC in TROPION-Lung01 [see Clinical Studies (14.1)], 360 patients with HR-positive, HER2-negative breast cancer in TROPION-Breast01 [see Clinical Studies (14.2)], and 50 patients with NSCLC and 83 patients with breast cancer in TROPION-PanTumor01 (NCT03401385). Among 927 patients who received DATROWAY, 45% were exposed for 6 months or longer and 19% were exposed for greater than one year. In this pooled safety population, the most common (≥20%) adverse reactions were stomatitis (63%), nausea (52%), fatigue (45%), alopecia (38%), constipation (28%), decreased appetite (23%), rash (23%), vomiting (22%), and musculoskeletal pain (20%). In this pooled safety population, the most common (≥2%) Grade 3 or 4 laboratory abnormalities were decreased lymphocytes (9%) and decreased hemoglobin (3.5%).

Locally Advanced or Metastatic EGFR-Mutated Non-Small Cell Lung Cancer

TROPION-Lung05, TROPION-Lung01, TROPION-PanTumor01

The safety of DATROWAY was evaluated in 125 patients with EGFR-mutated NSCLC who received DATROWAY 6 mg/kg administered as an intravenous infusion once every 3 weeks (21-day cycle) until disease progression or unacceptable toxicity in TROPION-Lung05 and TROPION-Lung01 [see Clinical Studies (14.1)] as well as TROPION-PanTumor01 (NCT03401385). Among these patients, the median duration of treatment was 6.1 months (range 0.7 months to 41.7 months).

The median age was 63 years (range: 36 to 81), 56% of patients were <65 years, 62% of patients were female; 66% were Asian, 26% were White, 0.8% were Black, 6% were other races; and 2.4% were of Hispanic ethnicity.

Serious adverse reactions occurred in 26% of patients who received DATROWAY. Serious adverse reactions in >1% of patients who received DATROWAY were COVID-19 (4%), stomatitis (2.4%), and pneumonia (1.6%). Fatal adverse reactions occurred in 1.6% of patients who received DATROWAY, due to death not otherwise specified.

Permanent discontinuation of DATROWAY due to an adverse reaction occurred in 8% of patients. Adverse reactions which resulted in permanent discontinuation of DATROWAY in >1% of patients included ILD/pneumonitis (2.4%) and abnormal hepatic function (1.6%).

Dosage interruptions of DATROWAY due to an adverse reaction occurred in 43% of patients. Adverse reactions which required dosage interruption in >1% of patients included COVID-19 (13%), stomatitis (7%), fatigue (6%), pneumonia (4%), anemia (2.4%), amylase increased (2.4%), keratitis (2.4%), ILD/pneumonitis (1.6%), decreased appetite (1.6%), dyspnea (1.6%), rash (1.6%), and infusion-related reaction (1.6%).

Dose reductions of DATROWAY due to an adverse reaction occurred in 26% of patients. Adverse reactions which required dose reduction in >1% of patients included stomatitis (14%), keratitis (1.6%), fatigue (1.6%), decreased weight (1.6%) and COVID-19 (1.6%).

The most common (≥20%) adverse reactions, including laboratory abnormalities, were stomatitis, nausea, alopecia, fatigue, decreased hemoglobin, decreased lymphocytes, constipation, increased calcium, increased AST, decreased white blood cell count, increased lactate dehydrogenase, musculoskeletal pain, decreased appetite, increased ALT, and rash.

Table 4: Adverse Reactions (≥10%) in Patients with Locally Advanced or Metastatic EGFR-Mutated NSCLC Who Received DATROWAY in TROPION-Lung05, TROPION-Lung01, and TROPION-PanTumor01
Adverse Reaction | DATROWAY N=125
Adverse Reaction | All Grades % | Grades 3 or 4 %
Gastrointestinal disorders
Stomatitis [Includes other related terms] | 71 | 9
Nausea | 50 | 0
Constipation | 31 | 0
Vomiting | 16 | 0.8
Diarrhea | 12 | 0
Skin and subcutaneous tissue disorders
Alopecia | 49 | 0
Rash | 20 | 0.8
Pruritus | 12 | 0
General disorders and administration site conditions
Fatigue [Includes fatigue, asthenia, and malaise] | 42 | 6
Musculoskeletal and connective tissue disorders
Musculoskeletal pain | 22 | 0.8
Metabolism and nutrition disorders
Decreased appetite | 20 | 1.6
Infections and Infestations
COVID-19 | 19 | 2.4
Respiratory, Thoracic, and Mediastinal Disorders
Cough | 18 | 0
Dyspnea | 11 | 2.4
Eye disorders
Dry eye | 13 | 0
Keratitis [Includes corneal disorder, corneal erosion, keratitis, punctate keratitis, and ulcerative keratitis] | 12 | 2.4
Injury, poisoning and procedural complications
Infusion-related reaction | 13 | 0
Nervous system disorders
Headache | 13 | 0
Events were graded using NCI CTCAE v5.0.

Clinically relevant adverse reactions occurring in <10% of patients who received DATROWAY included dry skin, blurred vision, abdominal pain, conjunctivitis, dry mouth, ILD/pneumonitis, skin hyperpigmentation, increased lacrimation, and visual impairment.

Table 5: Select Laboratory Abnormalities (≥20%) that Worsened from Baseline in Patients with Locally Advanced or Metastatic EGFR-Mutated NSCLC Who Received DATROWAY in TROPION-Lung05, TROPION-Lung01, and TROPION-PanTumor01
Laboratory Abnormality [Frequencies were based on NCI CTCAE v5.0 grade-derived laboratory abnormalities.] | DATROWAY [The denominator used to calculate the rate varied from 115 to 124 based on the number of patients with a baseline value and at least one post-treatment value.]
Laboratory Abnormality [Frequencies were based on NCI CTCAE v5.0 grade-derived laboratory abnormalities.] | All Grades % | Grades 3 or 4 %
Hematology
Decreased hemoglobin | 34 | 4.8
Decreased lymphocytes | 32 | 11
Decreased white blood cell count | 27 | 1.6
Chemistry
Increased calcium | 31 | 0
Increased AST | 28 | 2.4
Increased lactate dehydrogenase | 23 | 0
Increased ALT | 20 | 2.4

Unresectable or Metastatic, HR-Positive, HER2-Negative Breast Cancer

TROPION-Breast01

The safety of DATROWAY was evaluated in 360 patients with unresectable or metastatic HR-positive, HER2-negative (IHC 0, IHC1+ or IHC2+/ISH-) breast cancer who received at least one dose of DATROWAY 6 mg/kg in TROPION-Breast01 [see Clinical Studies (14.2)]. DATROWAY was administered by intravenous infusion once every three weeks. The median duration of treatment was 6.7 months (range: 0.7 months to 16.1 months) for patients who received DATROWAY.

Serious adverse reactions occurred in 15% of patients who received DATROWAY. Serious adverse reactions in >0.5% of patients who received DATROWAY were urinary tract infection (1.9%), COVID-19 infection (1.7%), ILD/pneumonitis (1.1%), acute kidney injury, pulmonary embolism, vomiting, diarrhea, hemiparesis, and anemia (0.6% each). Fatal adverse reactions occurred in 0.3% of patients who received DATROWAY and were due to ILD/pneumonitis.

Permanent discontinuation of DATROWAY due to an adverse reaction occurred in 3.1% of patients. Adverse reactions which resulted in permanent discontinuation of DATROWAY in >0.5% of patients included ILD/pneumonitis (1.7%) and fatigue (0.6%).

Dosage interruptions of DATROWAY due to an adverse reaction occurred in 22% of patients. Adverse reactions which required dosage interruption in >1% of patients included COVID-19 (3.3%), infusion-related reaction (1.4%), ILD/pneumonitis (1.9%), stomatitis (1.9%), fatigue (1.7%), keratitis (1.4%), acute kidney injury (1.1%), and pneumonia (1.1%).

Dose reductions of DATROWAY due to an adverse reaction occurred in 23% of patients. Adverse reactions which required dose reduction in >1% of patients included stomatitis (13%), fatigue (3.1%), nausea (2.5%), and weight decrease (1.9%).

The most common (≥20%) adverse reactions, including laboratory abnormalities, were stomatitis, nausea, fatigue, decreased leukocytes, decreased calcium, alopecia, decreased lymphocytes, decreased hemoglobin, constipation, decreased neutrophils, dry eye, vomiting, increased ALT, keratitis, increased AST, and increased alkaline phosphatase.

Table 6: Adverse Reactions (≥10%) in Patients Who Received DATROWAY in TROPION-Breast01
Adverse Reactions | DATROWAY N=360 |  | Chemotherapy N=351
Adverse Reactions | All Grades % | Grades 3 or 4 % | All Grades % | Grades 3 or 4 %
Gastrointestinal Disorders
Stomatitis [Includes other related terms.] | 59 | 7 | 17 | 2.6
Nausea | 56 | 1.4 | 27 | 0.6
Constipation | 34 | 0.3 | 17 | 0
Vomiting | 24 | 1.1 | 12 | 1.1
Diarrhea | 11 | 0.6 | 19 | 1.4
Abdominal pain | 11 | 0.6 | 15 | 1.4
General Disorders and Administration Site Conditions
Fatigue [Includes fatigue, asthenia, lethargy, malaise] | 44 | 4.2 | 40 | 3.7
Skin and Subcutaneous Tissue Disorders
Alopecia | 38 | 0 | 22 | 0
Rash | 19 | 0 | 17 | 2.3
Eye Disorders
Dry eye | 27 | 0.8 | 13 | 0
Keratitis [Includes corneal disorder, corneal erosion, corneal infiltrates, corneal lesion, corneal toxicity, injury corneal, keratitis, keratopathy, punctate keratitis, and ulcerative keratitis] | 24 | 1.1 | 10 | 0
Metabolism and Nutrition Disorders
Decreased appetite | 16 | 1.4 | 16 | 0.9
Infections and Infestations
COVID-19 | 16 | 1.4 | 13 | 0.9
Respiratory, Thoracic, and Mediastinal Disorders
Cough | 15 | 0 | 10 | 0
Events were graded using NCI CTCAE v5.0.

Clinically relevant adverse reactions occurring in <10% of patients who received DATROWAY included infusion-related reactions (including bronchospasm), ILD/pneumonitis, headache, pruritus, dry skin, dry mouth, conjunctivitis, blepharitis, meibomian gland dysfunction, blurred vision, increased lacrimation, photophobia, visual impairment, skin hyperpigmentation, and madarosis.

Table 7: Select Laboratory Abnormalities (≥20%) in Patients Who Received DATROWAY in TROPION-Breast01
Laboratory Abnormality | DATROWAY [The denominator used to calculate the rate varied from 264 to 359 based on the number of patients with a baseline value and at least one post-treatment value.] |  | Chemotherapy
Laboratory Abnormality | All Grades % | Grades 3-4 % | All Grades % | Grades 3-4 %
Hematology
Decreased leukocytes | 41 | 1.1 | 63 | 18
Decreased lymphocytes | 36 | 9 | 42 | 11
Decreased hemoglobin | 35 | 2.8 | 51 | 4.4
Decreased neutrophils | 30 | 1.6 | 61 | 35
Chemistry
Decreased calcium | 39 | 1.4 | 43 | 1.2
Increased AST | 23 | 1.9 | 28 | 0.9
Increased ALT | 24 | 1.7 | 31 | 0.6
Increased alkaline phosphatase | 23 | 0.6 | 20 | 0.6
Frequencies were based on NCI CTCAE v5.0 grade-derived laboratory abnormalities.

8 USE IN SPECIFIC POPULATIONS

8.1 Pregnancy

Risk Summary

Based on its mechanism of action, DATROWAY can cause embryo-fetal harm when administered to a pregnant woman because the topoisomerase inhibitor component of DATROWAY, DXd, is genotoxic and affects actively dividing cells [see Clinical Pharmacology (12.1), Nonclinical Toxicology (13.1)]. There are no available data on the use of DATROWAY in pregnant women to inform a drug-associated risk. Advise patients of the potential risks to a fetus.

In the U.S. general population, the estimated background risk of major birth defects and miscarriage in clinically recognized pregnancies is 2 to 4% and 15 to 20%, respectively.

Data

Animal Data

There were no animal reproductive or developmental toxicity studies conducted with datopotamab deruxtecan-dlnk.

8.2 Lactation

Risk Summary

There are no data regarding the presence of datopotamab deruxtecan-dlnk or its metabolites in human milk, the effects on the breastfed child, or the effects on milk production. Because of the potential for serious adverse reactions in a breastfed child, advise women not to breastfeed during treatment with DATROWAY and for 1 month after the last dose.

8.3 Females and Males of Reproductive Potential

DATROWAY can cause embryo-fetal harm when administered to a pregnant woman [see Use in Specific Populations (8.1)].

Pregnancy Testing

Verify pregnancy status of females of reproductive potential prior to initiation of DATROWAY.

Contraception

Females

Advise females of reproductive potential to use effective contraception during treatment with DATROWAY and for 7 months after the last dose.

Males

Because of the potential for genotoxicity, advise male patients with female partners of reproductive potential to use effective contraception during treatment with DATROWAY and for 4 months after the last dose [see Nonclinical Toxicology (13.1)].

Infertility

Based on findings in animal toxicity studies, DATROWAY may impair male and female reproductive function and fertility. The effects on reproductive organs in animals were irreversible [see Nonclinical Toxicology (13.1)].

8.4 Pediatric Use

Safety and effectiveness of DATROWAY have not been established in pediatric patients.

8.5 Geriatric Use

Of the 125 patients with EGFR-mutated NSCLC in TROPION-Lung05, TROPION-Lung01, TROPION-PanTumor01 treated with DATROWAY 6 mg/kg, 44% were ≥65 years of age and 10% were ≥75 years of age. No clinically meaningful differences in efficacy and safety were observed between patients ≥65 years of age versus younger patients.

Of the 365 patients in TROPION-Breast01 treated with DATROWAY 6 mg/kg, 25% were ≥65 years of age and 5% were ≥75 years of age. Grade ≥3 and serious adverse reactions were more common in patients ≥65 years (42% and 25%, respectively) compared to patients <65 years (33% and 15%, respectively). In TROPION-Breast01, no other meaningful differences in safety or efficacy were observed between patients ≥65 years of age versus younger patients.

8.6 Renal Impairment

A higher incidence of ILD/pneumonitis has been observed in patients with mild and moderate renal impairment (creatinine clearance [CLcr] 30 to <90 mL/min) [see Warnings and Precautions (5.1)]. Monitor patients with renal impairment for increased adverse reactions, including respiratory reactions. No dosage adjustment is recommended in patients with mild to moderate renal impairment [see Clinical Pharmacology (12.3)]. The effect of severe renal impairment (CLcr <30 mL/min) on the pharmacokinetics of datopotamab deruxtecan-dlnk or DXd is unknown.

8.7 Hepatic Impairment

No dosage adjustment is recommended in patients with mild hepatic impairment (total bilirubin ≤ULN and any AST >ULN or total bilirubin >1 to 1.5 times ULN and any AST). Limited data are available in patients with moderate hepatic impairment (total bilirubin >1.5 to 3 times ULN and any AST). Monitor patients with moderate hepatic impairment for increased adverse reactions [see Dosage and Administration (2.4)]. The recommended dosage of DATROWAY has not been established for patients with severe hepatic impairment (total bilirubin >3 times ULN and any AST) [see Clinical Pharmacology (12.3)].

11 DESCRIPTION

Datopotamab deruxtecan-dlnk is a Trop-2-directed antibody and topoisomerase inhibitor conjugate. Datopotamab deruxtecan-dlnk is an antibody-drug conjugate (ADC) composed of three components: 1) a humanized anti-Trop-2 IgG1 monoclonal antibody (mAb), covalently linked to 2) a topoisomerase I inhibitor, via 3) a tetrapeptide-based cleavable linker. Deruxtecan is composed of a protease-cleavable maleimide tetrapeptide linker and the topoisomerase inhibitor, DXd, which is an exatecan derivative.

The antibody is produced in Chinese hamster ovary cells by recombinant DNA technology, and the topoisomerase inhibitor and linker are produced by chemical synthesis. Approximately 4 molecules of deruxtecan are attached to each antibody molecule. Datopotamab deruxtecan-dlnk has the following structure:

DATROWAY (datopotamab deruxtecan-dlnk) for injection is a sterile, white to yellowish white, preservative-free lyophilized powder in single-dose vials. Each vial delivers 100 mg of datopotamab deruxtecan-dlnk, L-histidine (3.88 mg), L-histidine hydrochloride monohydrate (5.25 mg), polysorbate 80 (1.50 mg), and sucrose (450 mg). Following reconstitution with 5 mL of Sterile Water for Injection, USP, the resulting concentration of datopotamab deruxtecan-dlnk is 20 mg/mL with a pH of 6.0. The resulting solution is administered by intravenous infusion following dilution.

12 CLINICAL PHARMACOLOGY

12.1 Mechanism of Action

Datopotamab deruxtecan-dlnk, is a Trop-2-directed antibody-drug conjugate. The antibody is a humanized anti-Trop2 IgG1. The small molecule, DXd, is a topoisomerase I inhibitor attached to the antibody by a cleavable linker. Following binding to Trop-2 on cells, including tumor cells, datopotamab deruxtecan-dlnk undergoes internalization and intracellular linker cleavage by lysosomal enzymes. Upon release, the membrane-permeable DXd causes DNA damage and apoptotic cell death. Datopotamab deruxtecan-dlnk had anti-tumor activity in mouse models of lung cancer including EGFR-mutated and breast cancer.

12.2 Pharmacodynamics

Datopotamab deruxtecan-dlnk time course of pharmacodynamic response is unknown.

Exposure-Response Relationships

A relationship between datopotamab deruxtecan-dlnk exposure and efficacy has not been fully characterized in breast cancer or EGFR-mutated NSCLC.

In the pooled population of NSCLC (including EGFR-mutated NSCLC) and breast cancer patients, higher datopotamab deruxtecan-dlnk systemic exposure is associated with a higher incidence rate of serious adverse reactions, dosage interruptions, dose reductions, stomatitis/oral mucositis, ocular adverse reactions, and Grade ≥3 adverse reactions.

Cardiac Electrophysiology

At datopotamab deruxtecan-dlnk doses up to 10 mg/kg (1.7 times the recommended dose), mean increase in the QTc interval >20 ms was not observed.

12.3 Pharmacokinetics

Datopotamab deruxtecan-dlnk and DXd exposure after the first dose of the approved recommended dosage of cycle 1 are provided in Table 8. Datopotamab deruxtecan-dlnk and released DXd maximum concentration (Cmax) and area under the time-concentration curve (AUC) increases proportionally over a dose range of 4 mg/kg to 10 mg/kg (approximately 0.7 to 1.7 times the approved recommended dosage). No clinically significant datopotamab deruxtecan-dlnk accumulation occurs between cycles 1 and 3.

Table 8: Datopotamab Deruxtecan-dlnk and DXd Mean (CV%) Exposure After the First Dose
PK Parameter | Datopotamab deruxtecan-dlnk | DXd
Cmax | 154 µg/mL (20%) | 2.8 ng/mL (58%)
AUC | 671 µg*day/mL (31%) | 18 ng*day/mL (43%)
Abbreviations: Cmax =maximum concentration; AUC =area under the time-concentration curve

Distribution

Datopotamab deruxtecan-dlnk mean steady state volume of distribution is 3.5 (23%) L.

DXd plasma protein binding is approximately 98% and the blood-to-plasma concentration ratio is 0.6 in vitro.

Elimination

The datopotamab deruxtecan-dlnk median elimination half-life (t1/2) is 4.8 days (1.0, 8.2) and the released DXd median apparent t1/2 is approximately 5.5 days (3.2, 8.8). The estimated datopotamab deruxtecan-dlnk clearance is 0.6 (31.5%) L/day.

Metabolism

Datopotamab deruxtecan-dlnk undergoes intracellular cleavage by lysosomal enzymes to release DXd.

The humanized Trop-2 IgG1 monoclonal antibody is expected to be degraded into small peptides and amino acids via catabolic pathways in the same manner as endogenous IgG.

In vitro, DXd is primarily metabolized by CYP3A4.

Specific Populations

The mean volume of distribution and clearance of datopotamab deruxtecan-dlnk and DXd increase with increasing body weight (36 kg to 156 kg).

No clinically significant differences in the pharmacokinetics of datopotamab deruxtecan-dlnk or DXd were observed based on age (26 to 86 years), race (Asian, White, or Black), sex, mild hepatic impairment (total bilirubin ≤ULN and any AST >ULN or total bilirubin >1 to 1.5 times ULN and any AST), or mild to moderate renal impairment (CLcr 30 to <90 mL/min).

The pharmacokinetics of datopotamab deruxtecan-dlnk in patients with moderate hepatic impairment (total bilirubin >1.5 to 3 times ULN and any AST) was comparable to patients with normal hepatic function (total bilirubin and AST ≤ULN). The steady state average DXd AUC was 2.4-fold higher in patients with moderate hepatic impairment compared to patients with normal hepatic function. The effect of severe hepatic impairment (total bilirubin >3 times ULN and any AST) or severe renal impairment (CLcr <30 mL/min) on datopotamab deruxtecan-dlnk or DXd pharmacokinetics is unknown.

Drug Interaction Studies

Clinical Studies and Model-Informed Approaches

No clinically significant differences in DXd pharmacokinetics were predicted when used concomitantly with itraconazole (strong CYP3A inhibitor) or ritonavir (dual OATP1B and CYP3A inhibitor).

In Vitro Studies

CYP450 Enzymes: DXd does not inhibit CYP1A2, CYP2B6, CYP2C8, CYP2C9, CYP2C19, CYP2D6, or CYP3A and does not induce CYP1A2, CYP2B6, or CYP3A.

UDP-Glucuronosyltransferase (UGT): DXd does not undergo significant metabolism by UGT enzymes.

Transporters Systems: DXd is a substrate of OATP1B1, OATP1B3, MATE2-K, P-gp, MRP1, and BCRP. DXd does not inhibit OAT1, OAT3, OCT1, OCT2, OATP1B1, OATP1B3, MATE1, MATE2-K, P-gp, BCRP, or BSEP transporters.

12.6 Immunogenicity

There is insufficient information from TROPION-Breast01, TROPION-Lung01, and TROPION-Lung05 to characterize the anti-drug antibody response to datopotamab deruxtecan-dlnk and the effects of anti-drug antibodies on pharmacokinetics, pharmacodynamics, safety, or effectiveness of datopotamab deruxtecan-dlnk products.

13 NONCLINICAL TOXICOLOGY

13.1 Carcinogenesis, Mutagenesis, Impairment of Fertility

Carcinogenicity studies have not been conducted with datopotamab deruxtecan-dlnk.

The topoisomerase inhibitor component of datopotamab deruxtecan-dlnk, DXd, was clastogenic in both an in vivo rat bone marrow micronucleus assay and an in vitro Chinese hamster lung chromosome aberration assay and was not mutagenic in an in vitro bacterial reverse mutation assay.

Dedicated fertility studies have not been conducted with datopotamab deruxtecan-dlnk. In a 3-month repeat-dose toxicity study, intravenous administration of datopotamab deruxtecan-dlnk once every 3 weeks in rats resulted in decreased weights in the testes and epididymides, degeneration of the germinal epithelium and atrophy of seminiferous tubules in testes, and cell debris, decreased number of sperm, and single-cell necrosis of the ductal epithelium in epididymides at 200 mg/kg (approximately 29 times the human recommended dose of 6 mg/kg based on AUC). Findings in female rats included increased atretic follicles in the ovary and single cell necrosis of mucosal epithelium in the vagina at 200 mg/kg. These findings, except for the lesions in the testis and epididymis, were not observed after a 2-month recovery period.

14 CLINICAL STUDIES

14.1 Locally Advanced or Metastatic EGFR-Mutated Non-Small Cell Lung Cancer

The efficacy of DATROWAY was evaluated in a pooled subgroup of patients with locally advanced or metastatic EGFR-mutated NSCLC who were enrolled across two clinical studies: TROPION-Lung05 and TROPION-Lung01.

TROPION-Lung05 (NCT04484142) was a global, multicenter, single-arm, open-label trial in patients with previously treated NSCLC with an actionable genomic alteration and TROPION-Lung01 (NCT04656652) was a global, multicenter, randomized, active-controlled, open-label trial in patients with previously treated NSCLC with or without an actionable genomic alteration. For both trials, eligible patients with EGFR-mutated NSCLC must have previously received an EGFR-directed therapy and platinum-based chemotherapy. Patients with a history of ILD/pneumonitis requiring treatment with steroids, ongoing ILD/pneumonitis, or clinically significant corneal disease at screening were ineligible. Patients who had brain metastases that were untreated and symptomatic were also ineligible. Patients received DATROWAY 6 mg/kg by intravenous infusion every 3 weeks until unacceptable toxicity or disease progression.

For the pooled efficacy population, the major efficacy outcome measure was overall response rate (ORR) by BICR per RECIST v1.1. An additional efficacy outcome was duration of response (DOR) by BICR.

Efficacy was assessed in 114 patients with EGFR-mutated NSCLC. The median age was 63 years (range 36 to 81); 43% were ≥65 years of age; 63% were female; 70% were Asian and 22% were White; 1.8% were of Hispanic/Latino ethnicity; 68% had ECOG PS of 1 and 32% had ECOG PS of 0; and 33% had brain metastases at baseline. Fifty-three percent (53%) of patients had tumors with exon 19 deletions, 34% had exon 21 L858R mutations, 28% had T790M mutations, 2.6% had exon 20 insertion mutations and 14% had other EGFR mutations. Four percent (4.4%) of patients received one prior line of systemic therapy, 39% received two prior lines of systemic therapy, and 57% received three or more prior lines of systemic therapy in the locally advanced or metastatic setting. All patients received prior EGFR-directed therapy including 84% receiving prior osimertinib; 99% received prior platinum-based chemotherapy and 28% received prior anti-PD-1/ PD-L1 therapy.

Efficacy results are summarized in Table 9.

Table 9: Efficacy Results in TROPION-Lung05 and TROPION-Lung01 by BICR
 | DATROWAY TL05 N=77 | DATROWAY TL01 N=37 | DATROWAY Pooled N=114
Overall Response Rate (95% CI) | 45% (34, 57) | 43% (27, 61) | 45% (35, 54)
Complete Response | 5% | 2.7% | 4.4%
Partial Response | 40% | 41% | 40%
Duration of Response Median, months (95% CI) | 6.9 (4.2, 10.2) | 6.5 (4.0, 8.4) | 6.5 (4.2, 8.4)
≥6 months | 49% | 44% | 47%
≥12 months | 23% | 6% | 18%
CI: confidence interval

In the TROPION-Lung05 trial, a difference was noted between ORR by BICR and ORR assessed by investigator; investigator assessed ORR was 34% (95% CI: 23, 45). In the TROPION-Lung01 trial, ORR assessed by investigator was similar to ORR by BICR.

14.2 Unresectable or Metastatic, HR-Positive, HER2-Negative Breast Cancer

TROPION-Breast01

The efficacy of DATROWAY was evaluated in TROPION-Breast01 (NCT05104866), a multicenter, open-label, randomized trial of 732 patients with unresectable or metastatic HR-positive, HER2-negative (IHC 0, IHC1+ or IHC2+/ISH-) breast cancer. Eligible patients must have progressed on and deemed not suitable for further endocrine therapy. Patients were required to have received 1 or 2 lines of prior chemotherapy in the unresectable or metastatic disease setting. Patients were excluded for a history of ILD/pneumonitis requiring treatment with steroids, ongoing ILD/pneumonitis, clinically active brain metastases, or clinically significant corneal disease at screening. Patients were also excluded for ECOG performance status >1. Randomization was stratified by previous lines of chemotherapy (one or two), prior treatment with a CDK4/6 inhibitor (yes or no), and geographical region.

A total of 732 patients were randomized 1:1 to receive either DATROWAY 6 mg/kg (N=365) by intravenous infusion every 3 weeks or investigator's choice of chemotherapy (N=367) until unacceptable toxicity or disease progression. Single agent chemotherapy was determined by the investigator before randomization from one of the following choices: eribulin (60%), capecitabine (21%), vinorelbine (10%), or gemcitabine (9%).

The major efficacy outcomes were progression-free survival (PFS) as assessed by blinded independent central review (BICR) based on Response Evaluation Criteria in Solid Tumors (RECIST) v.1.1 and overall survival (OS). Additional efficacy outcomes included confirmed objective response rate (ORR) and duration of response (DOR) by BICR.

The median age was 55 years (range 28-86); 22% were ≥65 years; 99% were female; 48% were White, 41% were Asian, 1.5% were Black or African American, and 11% were of Hispanic/Latino ethnicity; 57% had ECOG PS of 0 and 42% had ECOG PS of 1; 97% had visceral disease, 72% had liver metastases, and 8% had stable brain metastases.

Sixty percent (60%) of patients received prior endocrine therapy in the (neo)adjuvant setting, and 89% received prior endocrine therapy in the unresectable or metastatic setting. Eighty-three percent (83%) of patients had prior treatment with a CDK4/6 inhibitor. All patients received prior chemotherapy regimens in the unresectable or metastatic setting (81% received prior taxanes; 64% received prior anthracyclines). Sixty-two percent (62%) of patients had 1 prior chemotherapy regimen and 38% of patients had 2 prior chemotherapy regimens for treatment of unresectable or metastatic disease.

The study demonstrated a statistically significant improvement in PFS in patients randomized to DATROWAY compared to chemotherapy.

Efficacy results are shown in Table 10 and Figure 1.

Table 10: Efficacy Results in TROPION-Breast01
 | DATROWAY (n=365) | Chemotherapy (n=367)
Progression-Free Survival [Assessed by BICR]
Number of events (%) | 212 (58) | 235 (64)
Progressive Disease | 201 (55) | 218 (59)
Death | 11 (3) | 17 (5)
Median, months (95% CI) | 6.9 (5.7, 7.4) | 4.9 (4.2, 5.5)
Hazard ratio (95% CI) [Based on the stratified Cox proportional hazards model] | 0.63 (0.52, 0.76)
p-value [Two-sided p-value based on stratified log-rank test.] , [p-value is compared with the allocated alpha of 0.01.] | < 0.0001
Overall Survival
Number of events (%) | 223 (61) | 213 (58)
Median, months (95% CI) | 18.6 (17.3, 20.1) | 18.3 (17.3, 20.5)
Hazard ratio (95% CI) | 1.01 (0.83, 1.22)
p-value | NS
Confirmed Objective Response Rate
n (%) | 133 (36) | 84 (23)
(95% CI) | 31, 42 | 19, 28
Complete Response n (%) | 2 (0.5) | 0
Partial Response n (%) | 131 (36) | 84 (23)
Duration of Response
Median, months (95% CI) | 6.7 (5.6, 9.8) | 5.7 (4.9, 6.8)
CI: Confidence interval; NS: not statistically significant

Figure 1: Kaplan-Meier Plot of PFS by BICR in TROPION-Breast-01

15 REFERENCES

1. OSHA Hazardous Drugs. OSHA. http://www.osha.gov/SLTC/hazardousdrugs/index.html

16 HOW SUPPLIED/STORAGE AND HANDLING

How Supplied

DATROWAY (datopotamab deruxtecan-dlnk) for injection is a white to yellowish white lyophilized powder supplied as:

Carton Contents | NDC
One 100 mg single-dose vial | NDC 65597-801-01

Storage and Handling

Store vials in a refrigerator at 2ºC to 8ºC (36ºF to 46ºF) in the original carton to protect from light until time of reconstitution. Do not freeze. Do not shake the reconstituted or diluted solution [see Dosage and Administration (2.5)].

DATROWAY (datopotamab deruxtecan-dlnk) is a hazardous drug. Follow applicable special handling and disposal procedures.^1

17 PATIENT COUNSELING INFORMATION

Advise the patient to read the FDA-approved patient labeling (Medication Guide).

Interstitial Lung Disease/Pneumonitis

- Inform patients of the risks of severe or fatal ILD. Advise patients to contact their healthcare provider immediately for any of the following: cough, shortness of breath, fever, or other new or worsening respiratory symptoms [see Warnings and Precautions (5.1)].

Ocular Adverse Reactions

- Inform patients about the need for eye exams at initiation and during treatment with DATROWAY [see Dosage and Administration (2.3)].
- Advise patients to contact their healthcare provider if they experience any eye symptoms [see Warnings and Precautions (5.2)].
- Advise patients to use preservative-free lubricating eye drops several times daily and to avoid use of contact lenses during treatment with DATROWAY [see Dosage and Administration (2.3, 2.4)].

Stomatitis

- Inform patients of the risk of stomatitis. Advise patients to contact their healthcare provider if they experience any symptoms.
- Inform patients to use a steroid-containing mouthwash for prophylaxis and treatment of stomatitis.
- Instruct patients to hold ice chips or ice water in their mouth throughout the infusion of DATROWAY [see Warnings and Precautions (5.3)].

Embryo-Fetal Toxicity

- Inform female patients of the potential risk to a fetus. Advise female patients to inform their healthcare provider of a known or suspected pregnancy [see Warnings and Precautions (5.4), Use in Specific Populations (8.1)].
- Advise females of reproductive potential to use effective contraception during treatment with DATROWAY and for 7 months after the last dose [see Use in Specific Populations (8.3)].
- Advise male patients with female partners of reproductive potential to use effective contraception during treatment with DATROWAY and for 4 months after the last dose [see Use in Specific Populations (8.3)].

Lactation

- Advise women not to breastfeed during treatment and for 1 month after the last dose of DATROWAY [see Use in Specific Populations (8.2)].

Infertility

- Advise males and females of reproductive potential that DATROWAY may impair fertility [see Use in Specific Populations (8.3)].

Manufactured by:
Daiichi Sankyo, Inc., Basking Ridge, NJ 07920

U.S. License No. 2128

Marketed by:
Daiichi Sankyo, Inc., Basking Ridge, NJ 07920 and AstraZeneca Pharmaceuticals LP, Wilmington, DE 19850

DATROWAY® is a registered trademark of Daiichi Sankyo Company, Ltd.
© 2025 Daiichi Sankyo Co., Ltd.

USPI-DAT-C7-0625-r002

MEDICATION GUIDE
DATROWAY® (DAT-roe-way)
(datopotamab deruxtecan-dlnk)
for injection, for intravenous use

What is the most important information I should know about DATROWAY?
DATROWAY can cause serious side effects, including:

- Lung problems that may be severe, life-threatening, or that may lead to death. If you develop lung problems your healthcare provider may treat you with corticosteroid medicines. Tell your healthcare provider right away if you get any of the following signs and symptoms:
  - cough
  - trouble breathing or shortness of breath
  - fever
  - other new or worsening breathing symptoms such as chest tightness or wheezing

- Eye problems. Eye problems are common with DATROWAY and can also be severe. Tell your healthcare provider right away if you develop any new or worsening eye problems during treatment with DATROWAY, including dry eyes, eye pain, eye redness, eye swelling, eye irritation, increased tears, feeling like something is in your eyes, discharge from your eyes, eye crusting, sensitivity to light, blurred vision, or vision changes.
  - You should use preservative-free lubricating eye drops at least 4 times a day and as needed.
  - Do not wear contact lenses during treatment with DATROWAY unless your eye specialist tells you to.
  - Your healthcare provider will send you to an eye specialist to check your eyes when you start your treatment with DATROWAY, every year during treatment, at the end of treatment, and as needed for any new or worsening signs and symptoms of eye problems.
- Mouth ulcers and sores. Mouth ulcers and sores are common with DATROWAY and can also be severe. Tell your healthcare provider right away if you develop mouth pain, swelling, redness, ulcers, or sores during treatment with DATROWAY.
  - Your healthcare provider will prescribe a steroid-containing mouthwash to use 4 times a day and as needed during treatment with DATROWAY.
  - You should hold ice chips or ice water in your mouth during your DATROWAY infusions.

Your healthcare provider will check you for these side effects during your treatment with DATROWAY. Your healthcare provider may reduce your dose, delay treatment, or completely stop treatment with DATROWAY if you have severe side effects.

- Harm to your unborn baby. Tell your healthcare provider right away if you become pregnant or think you might be pregnant during treatment with DATROWAY.
  - If you are able to become pregnant, your healthcare provider should do a pregnancy test before you start treatment with DATROWAY.
  - Females who are able to become pregnant should use effective birth control (contraception) during treatment with DATROWAY and for 7 months after the last dose.
  - Males who have female partners that are able to become pregnant should use effective birth control (contraception) during treatment with DATROWAY and for 4 months after the last dose.

See "What are the possible side effects of DATROWAY?" for more information about side effects.

What is DATROWAY?
DATROWAY is a prescription medicine used to treat adults who have:

- non-small cell lung cancer (NSCLC) that has certain mutations in a gene called epidermal growth factor receptor (EGFR):
  - that has spread to areas outside of the lung (locally advanced) or has spread to other parts of the body (metastatic), and
  - who have received prior EGFR-directed medicine and platinum-based chemotherapy.
- hormone receptor (HR)-positive and human epidermal growth factor receptor 2 (HER2)-negative breast cancer:
  - that cannot be removed by surgery (unresectable) or has spread to other parts of the body (metastatic), and
  - who have received prior endocrine-based therapy and chemotherapy treatment for unresectable or metastatic disease.

It is not known if DATROWAY is safe and effective in children.

Before receiving DATROWAY, tell your healthcare provider about all of your medical conditions, including if you:

- have lung or breathing problems.
- have eye problems.
- use contact lenses.
- are breastfeeding or plan to breastfeed. It is not known if DATROWAY passes into your breast milk. Do not breastfeed during treatment with DATROWAY and for 1 month after the last dose.

Tell your healthcare provider about all the medicines you take, including prescription and over-the-counter medicines, vitamins, and herbal supplements.

How will I receive DATROWAY?

- You will receive DATROWAY into your vein through an intravenous (IV) line by your healthcare provider.
- DATROWAY is usually given 1 time every three weeks (21-day treatment cycle).
- You will receive your first infusion over 90 minutes. If you do not have problems with your first infusion, you may receive your next infusions over 30 minutes.
- You will be monitored for side effects for at least 1 hour after your first 2 infusions. If you do not have problems after your second infusion, you will be monitored for at least 30 minutes after each following infusion.
- Your healthcare provider will decide how many treatments you need.
- Your healthcare provider will give you medicines before your infusion to help prevent nausea, vomiting, and infusion-related reactions.
- Your healthcare provider may slow down or temporarily stop your infusion of DATROWAY if you have an infusion-related reaction, or permanently stop DATROWAY if you have severe infusion reactions.
- If you miss a planned dose of DATROWAY, call your healthcare provider right away to schedule an appointment. Do not wait until the next planned treatment cycle.

What are the possible side effects of DATROWAY?
DATROWAY can cause serious side effects, including:

- See "What is the most important information I should know about DATROWAY?"

The most common side effects of DATROWAY when used in adults with EGFR-mutated non-small cell lung cancer include:

- nausea
- hair loss
- tiredness
- decreased red blood cell counts
- decreased white blood cell counts
- constipation
- increased blood levels of calcium

- increased blood levels of liver enzymes
- increased levels of enzyme called lactate dehydrogenase in the blood
- muscle and joint pain
- rash
- decreased appetite

The most common side effects of DATROWAY when used in adults with HR-positive HER2-negative breast cancer include:

- nausea
- tiredness
- decreased white blood cell counts
- decreased blood levels of calcium
- hair loss
- decreased red blood cell counts
- constipation

- dry eye
- vomiting
- increased blood levels of liver enzymes
- an eye problem called keratitis. See "What is the most important information I should know about DATROWAY?"
- increased blood levels of alkaline phosphatase

DATROWAY may cause fertility problems in males and females, which may affect your ability to have children. Talk to your healthcare provider if you have concerns about fertility.
These are not all of the possible side effects of DATROWAY.
Call your doctor for medical advice about side effects. You may report side effects to FDA at 1-800-FDA-1088.

General information about the safe and effective use of DATROWAY.
Medicines are sometimes prescribed for purposes other than those listed in a Medication Guide. You can ask your pharmacist or healthcare provider for information about DATROWAY that is written for health professionals.

What are the ingredients in DATROWAY?
Active ingredient: datopotamab deruxtecan-dlnk
Inactive ingredients: L-histidine, L-histidine hydrochloride monohydrate, polysorbate 80, and sucrose
Manufactured by: Daiichi Sankyo, Inc., Basking Ridge, NJ 07920
U.S. License No. 2128
Marketed by: Daiichi Sankyo, Inc., Basking Ridge, NJ 07920 and AstraZeneca Pharmaceuticals LP, Wilmington, DE 19850
DATROWAY® is a registered trademark of Daiichi Sankyo Company, Ltd.
© 2025 Daiichi Sankyo Co., Ltd.
USMG-DAT-C7-0625-r002
For more information, call 1-877-437-7763 or go to https://www.DATROWAY.com.

This Medication Guide has been approved by the U.S. Food and Drug Administration.

Revised: 06/2025

PRINCIPAL DISPLAY PANEL - 100 mg Vial Carton

NDC 65597-801-01
Rx only

DATROWAY®
(datopotamab deruxtecan-dlnk)
For Injection

100 mg per vial

For Intravenous Infusion Only

Reconstitute and dilute prior to administration.

Single-dose vial. Discard unused portion.

Dispense the enclosed Medication Guide to
each patient.

Hazardous Drug

KEEP REFRIGERATED
1 vial

Daiichi-Sankyo
AstraZeneca